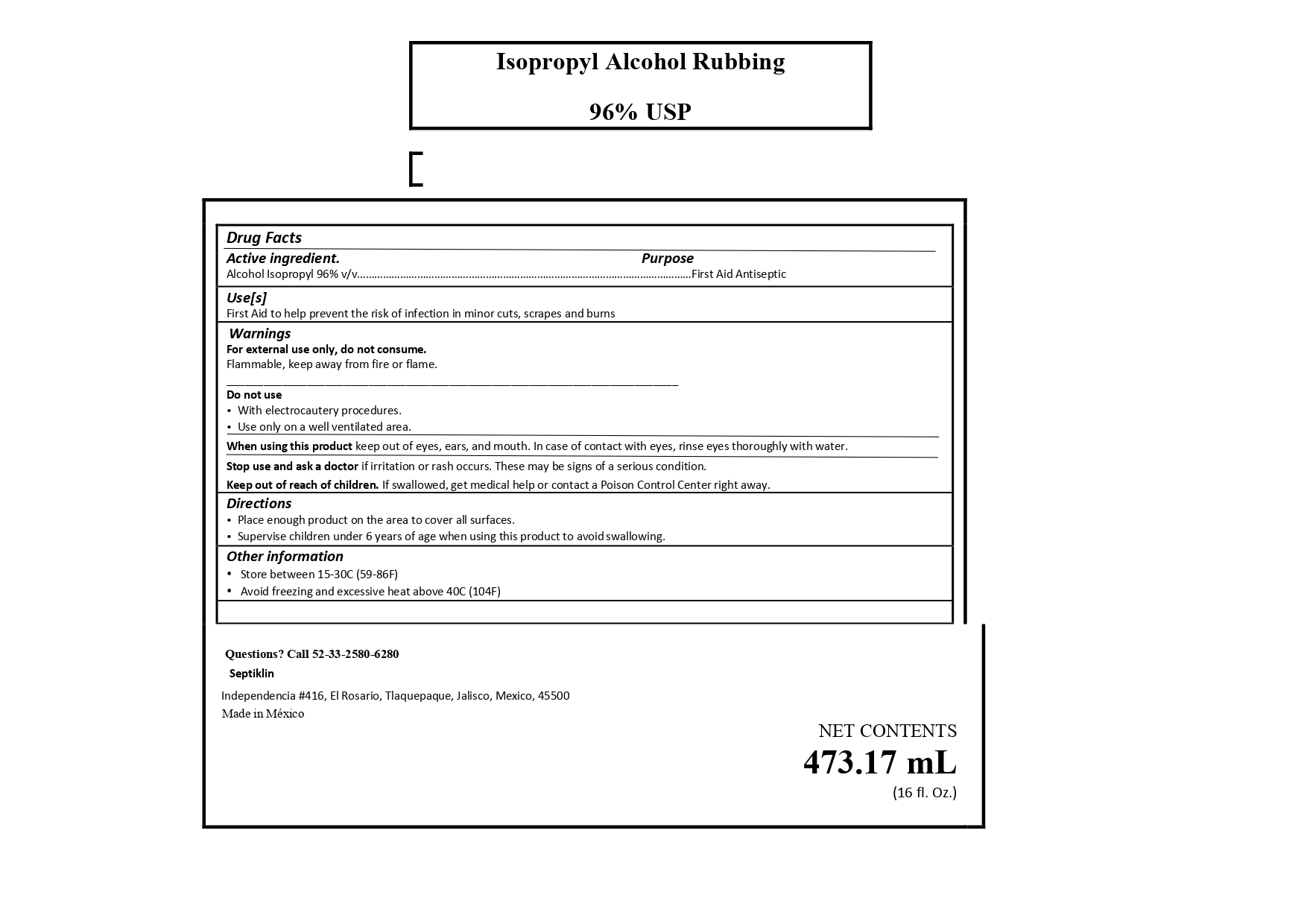 DRUG LABEL: Alcohol
NDC: 77196-004 | Form: LIQUID
Manufacturer: Ignacio Reyes Gonzalez
Category: otc | Type: HUMAN OTC DRUG LABEL
Date: 20200610

ACTIVE INGREDIENTS: ALCOHOL 100 mL/100 mL
INACTIVE INGREDIENTS: WATER 10 mL/100 mL

This is a Isorpopyl Alcohol manufactured according to the Temporary Policy for Preparation of Certain Alcohol-Based Hand Sanitizer Products During the Public Health Emergency (CoViD-19); Guidance for Industry.

The Isopropyl Alcohol is manufactured using only the following United States Pharmacopoeia (USP) grade ingredients in the preparation of the product (percentage in final product formulation) consistent with World Health Organization (WHO) recommendations:

1. Isopropyl Alcohol (USP or Food Chemical Codex (FCC) grade) (96%, volume/volume (v/v)) in an liquid solution denatured

The firm does not add other active or inactive ingredients. Different or additional ingredients may impact the quality and potency of the product.

Active Ingredient(s)

Alcohol 96% v/v. Purpose: First aid Antiseptic

Purpose

First Aid Antiseptic

Use

First aid to help prevent the risk of infection in minor cuts, scrapes and burns.

Warnings

For external use only. Flammable. Keep away from heat or flame

- do not use with electricautery procedures

When using this product keep out of eyes, ears, and mouth. In case of contact with eyes, rinse eyes thoroughly with water.
Stop use and ask a doctor if irritation or rash occurs. These may be signs of a serious condition.
Keep out of reach of children. If swallowed, get medical help or contact a Poison Control Center right away.

Stop use and ask a doctor if irritation or rash occurs. These may be signs of a serious condition.

Keep out of reach of children. If swallowed, get medical help or contact a Poison Control Center right away.

Directions

- Clean the affected area, apply small amount of this product 1 to 3 times daily.
- May be covered with a sterile bandaged, let dry first.

Other information

- Store between 15-30C (59-86F)
- Avoid freezing and excessive heat above 40C (104F)

Inactive Ingredient

Purified Water

Package Label - Principal Display Panel

743 mL NDC: 77196-004-01